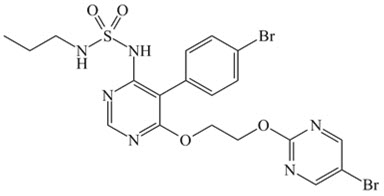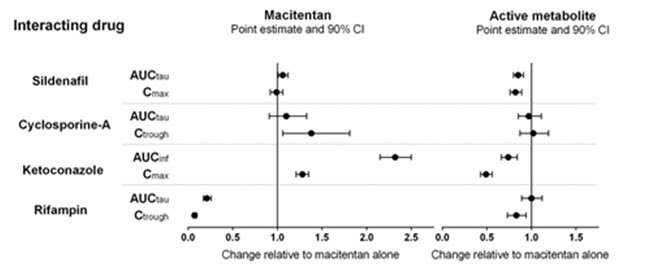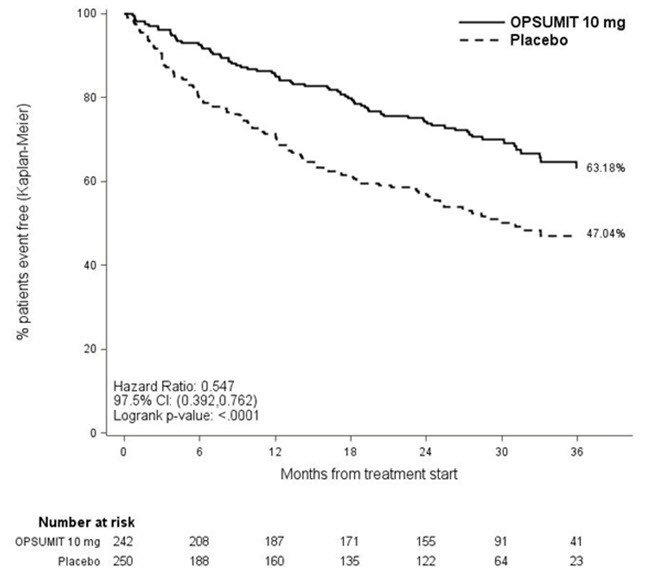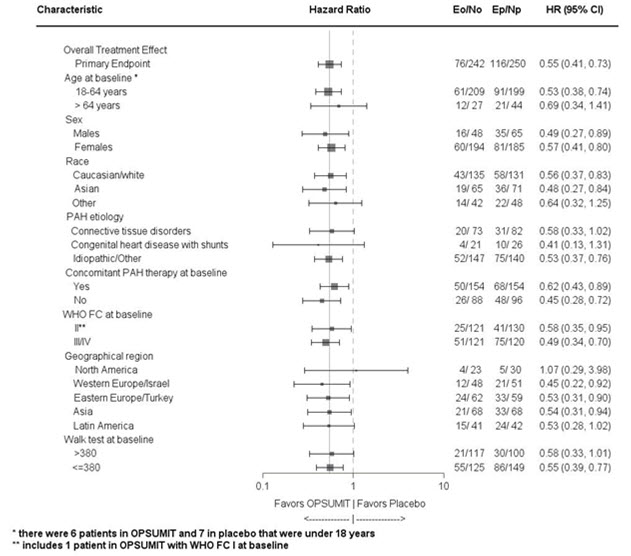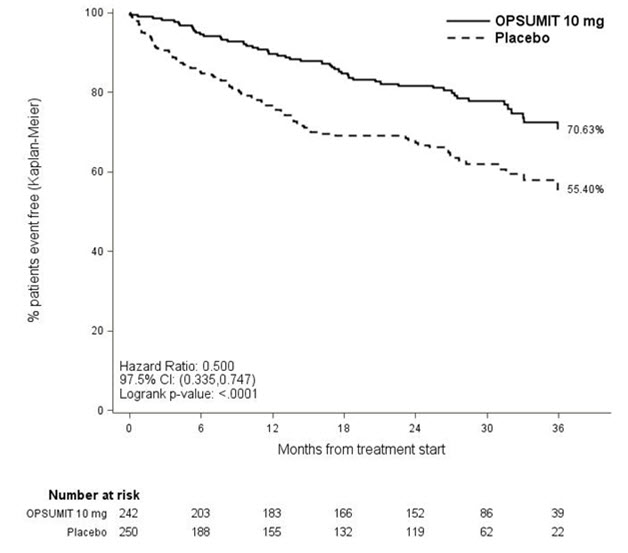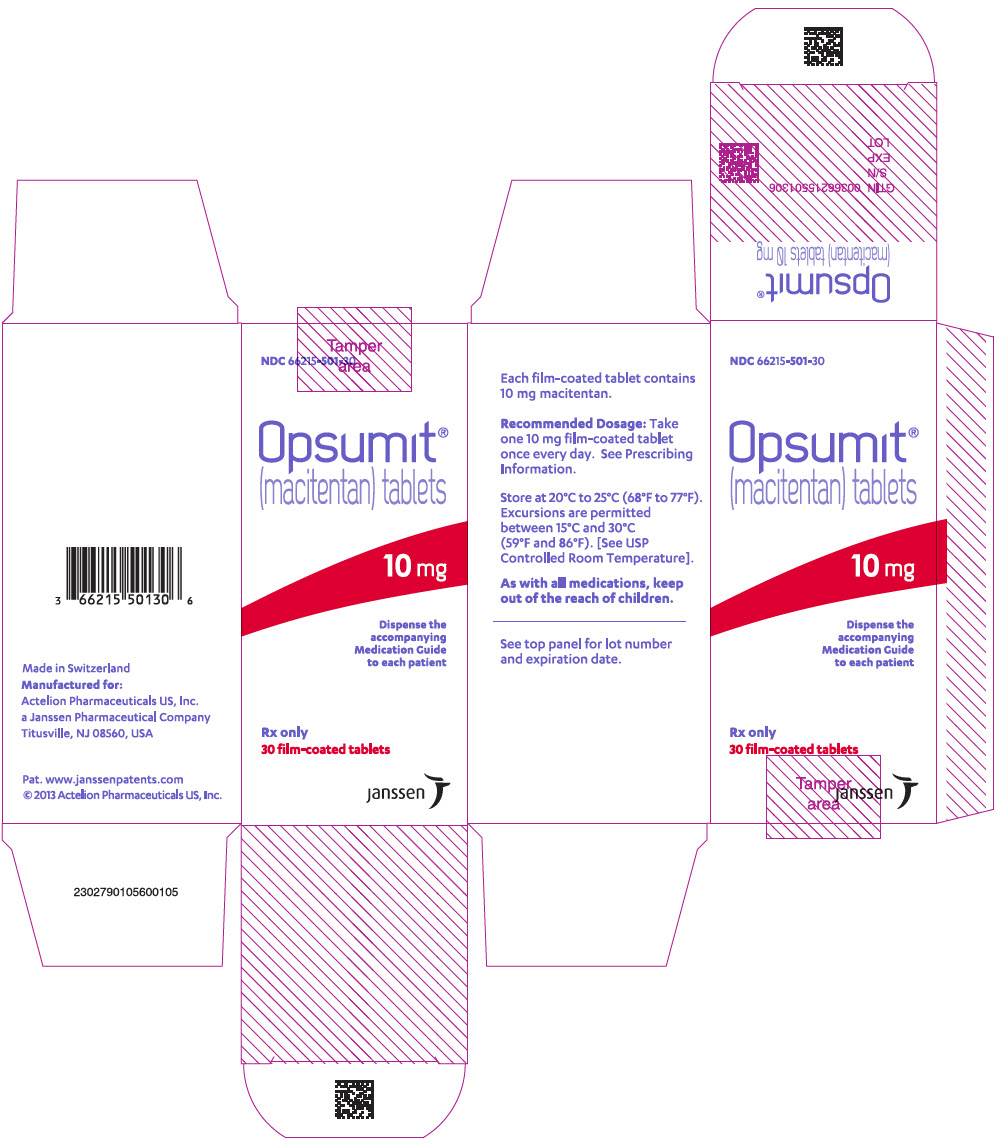 DRUG LABEL: OPSUMIT
NDC: 66215-501 | Form: TABLET, FILM COATED
Manufacturer: Actelion Pharmaceuticals US, Inc.
Category: prescription | Type: HUMAN PRESCRIPTION DRUG LABEL
Date: 20250411

ACTIVE INGREDIENTS: MACITENTAN 10 mg/1 1
INACTIVE INGREDIENTS: LACTOSE MONOHYDRATE; MICROCRYSTALLINE CELLULOSE; SODIUM STARCH GLYCOLATE TYPE A POTATO; POVIDONE, UNSPECIFIED; MAGNESIUM STEARATE; POLYSORBATE 80; POLYVINYL ALCOHOL, UNSPECIFIED; SOYBEAN LECITHIN; TALC; TITANIUM DIOXIDE; XANTHAN GUM

HIGHLIGHTS OF PRESCRIBING INFORMATION

These highlights do not include all the information needed to use OPSUMIT safely and effectively. See full prescribing information for OPSUMIT.
OPSUMIT®(macitentan) tablets, for oral use
Initial U.S. Approval: 2013

WARNING: EMBRYO-FETAL TOXICITY

See full prescribing information for complete boxed warning.

- Based on animal data, OPSUMIT may cause fetal harm if used during pregnancy (4.1, 5.1, 8.1).
- Females of reproductive potential: exclude pregnancy before start of treatment. Prevent pregnancy prior to initiation of treatment, during treatment and for one month after treatment by using effective methods of contraception (2.2, 8.3).
- When pregnancy is detected, discontinue OPSUMIT as soon as possible (5.1).

RECENT MAJOR CHANGES

Boxed Warning | 4/2025
Dosage and Administration (2.2) | 4/2025
Warnings and Precautions (5.1) | 4/2025
Warnings and Precautions (5.2) | Removal 4/2025

1 INDICATIONS AND USAGE

OPSUMIT is an endothelin receptor antagonist (ERA) indicated for the treatment of pulmonary arterial hypertension (PAH, WHO Group I) in adults to reduce the risks of disease progression and hospitalization for PAH (1.1).

2 DOSAGE AND ADMINISTRATION

- 10 mg once daily .Doses higher than 10 mg once daily have not been studied in patients with PAH and are not recommended (2.1).

3 DOSAGE FORMS AND STRENGTHS

- Tablet: 10 mg (3)

4 CONTRAINDICATIONS

- Pregnancy (4.1)
- Hypersensitivity (4.2)

5 WARNINGS AND PRECAUTIONS

- ERAs cause hepatotoxicity and liver failure. Obtain baseline liver enzymes and monitor as clinically indicated (5.2).
- Fluid retention may require intervention (5.3).
- Decreases in hemoglobin (5.4).
- Pulmonary edema in patients with pulmonary veno-occlusive disease. If confirmed, discontinue treatment (5.5).
- Decreases in sperm count have been observed in patients taking ERAs (5.6).

6 ADVERSE REACTIONS

Most common adverse reactions (more frequent than placebo by ≥3%) are anemia, nasopharyngitis/pharyngitis, bronchitis, headache, influenza, and urinary tract infection (6.1).

To report SUSPECTED ADVERSE REACTIONS, contact Actelion at 1-800-526-7736 or FDA at 1-800-FDA-1088 or www.fda.gov/medwatch.

7 DRUG INTERACTIONS

- Strong CYP3A4 inducers (rifampin) reduce exposure to macitentan: avoid co-administration with OPSUMIT (7.1, 12.3).
- Strong CYP3A4 inhibitors (ketoconazole, ritonavir) increase exposure to macitentan: avoid co-administration with OPSUMIT (7.2, 12.3) .
- Moderate dual CYP3A4 and CYP2C9 inhibitors (fluconazole, amiodarone) or use of combined CYP3A4 and CYP2C9 inhibitors may increase exposure to macitentan: avoid co-administration with OPSUMIT (7.3, 12.3).

8 USE IN SPECIFIC POPULATIONS

- Lactation: Advise not to breastfeed. (8.2)

FULL PRESCRIBING INFORMATION

WARNING: EMBRYO-FETAL TOXICITY

OPSUMIT is contraindicated for use during pregnancy because it may cause fetal harm based on animal data [see Contraindications (4.1), Warnings and Precautions (5.1), Use in Specific Populations (8.1)].

Therefore, for females of reproductive potential, exclude pregnancy before the start of treatment with OPSUMIT. Advise use of effective contraception before the initiation of treatment, during treatment, and for one month after stopping treatment with OPSUMIT [see Dosage and Administration (2.2), Use in Specific Populations (8.3)]. When pregnancy is detected, discontinue OPSUMIT as soon as possible [see Warnings and Precautions (5.1)].

1 INDICATIONS AND USAGE

1.1 Pulmonary Arterial Hypertension

OPSUMIT is an endothelin receptor antagonist (ERA) indicated for the treatment of pulmonary arterial hypertension (PAH, WHO Group I) in adults to reduce the risks of disease progression and hospitalization for PAH.

Effectiveness was established in a long-term study in PAH patients with predominantly WHO Functional Class II–III symptoms treated for an average of 2 years. Patients had idiopathic and heritable PAH (57%), PAH caused by connective tissue disorders (31%), and PAH caused by congenital heart disease with repaired shunts (8%) [see Clinical Studies (14.1)] .

2 DOSAGE AND ADMINISTRATION

2.1 Recommended Dosage

The recommended dosage of OPSUMIT is 10 mg once daily for oral administration. Doses higher than 10 mg once daily have not been studied in patients with PAH and are not recommended.

2.2 Pregnancy Testing in Females of Reproductive Potential

Exclude pregnancy before initiating treatment with OPSUMIT in females of reproductive potential [see Boxed Warning, Contraindications (4.1), Warnings and Precautions (5.1), and Use in Specific Populations (8.3)] .

3 DOSAGE FORMS AND STRENGTHS

Tablets: 10 mg, bi-convex film-coated, round, white, and debossed with "10" on both sides.

4 CONTRAINDICATIONS

4.1 Pregnancy

OPSUMIT may cause fetal harm when administered to a pregnant woman. OPSUMIT is contraindicated in females who are pregnant. OPSUMIT was consistently shown to have teratogenic effects when administered to animals. If OPSUMIT is used during pregnancy, advise the patient of the potential risk to a fetus [see Warnings and Precautions (5.1)and Use in Specific Populations (8.1)] .

4.2 Hypersensitivity

OPSUMIT is contraindicated in patients with a history of a hypersensitivity reaction to macitentan or any component of the product [see Adverse Reactions (6.2)] .

5 WARNINGS AND PRECAUTIONS

5.1 Embryo-fetal Toxicity

Based on data from animal reproduction studies, OPSUMIT may cause fetal harm when administered to a pregnant patient and is contraindicated during pregnancy. The available human data for ERAs do not establish the presence or absence of major birth defects related to the use of OPSUMIT. Advise patients who can become pregnant of the potential risk to a fetus. Obtain a pregnancy test prior to initiation of therapy with OPSUMIT. Advise patients who can become pregnant to use effective contraceptive methods prior to initiation of treatment, during treatment, and for one month after discontinuation of treatment with OPSUMIT. When pregnancy is detected, discontinue use as soon as possible [see Dosage and Administration (2.2), Contraindications (4.1), and Use in Specific Populations (8.1, 8.3)] .

5.2 Hepatotoxicity

ERAs have caused elevations of aminotransferases, hepatotoxicity, and liver failure. The incidence of elevated aminotransferases in the study of OPSUMIT in PAH is shown in Table 1.

Table 1: Incidence of Elevated Aminotransferases in the SERAPHIN Study
 | OPSUMIT 10 mg (N=242) | Placebo (N=249)
>3 × ULN | 3.4% | 4.5%
>8 × ULN | 2.1% | 0.4%

In the placebo-controlled study of OPSUMIT, discontinuations for hepatic adverse events were 3.3% in the OPSUMIT 10 mg group vs. 1.6% for placebo.

Obtain liver enzyme tests prior to initiation of OPSUMIT and repeat during treatment as clinically indicated [see Adverse Reactions (6.2)] .

Advise patients to report symptoms suggesting hepatic injury (nausea, vomiting, right upper quadrant pain, fatigue, anorexia, jaundice, dark urine, fever, or itching). If clinically relevant aminotransferase elevations occur, or if elevations are accompanied by an increase in bilirubin >2 × ULN, or by clinical symptoms of hepatotoxicity, discontinue OPSUMIT. Consider re-initiation of OPSUMIT when hepatic enzyme levels normalize in patients who have not experienced clinical symptoms of hepatotoxicity.

5.3 Fluid Retention

Peripheral edema and fluid retention are known clinical consequences of PAH and known effects of ERAs. In the placebo-controlled study of OPSUMIT in PAH, the incidence of edema was 21.9% in the OPSUMIT 10 mg group and 20.5% in the placebo group.

Patients with underlying left ventricular dysfunction may be at particular risk for developing significant fluid retention after initiation of ERA treatment. In a small study of OPSUMIT in patients with pulmonary hypertension because of left ventricular dysfunction, more patients in the OPSUMIT group developed significant fluid retention and had more hospitalizations because of worsening heart failure compared to those randomized to placebo. Postmarketing cases of edema and fluid retention occurring within weeks of starting OPSUMIT, some requiring intervention with a diuretic or hospitalization for decompensated heart failure, have been reported [see Adverse Reactions (6.2)] .

Monitor for signs of fluid retention after OPSUMIT initiation. If clinically significant fluid retention develops, evaluate the patient to determine the cause, such as OPSUMIT or underlying heart failure, and the possible need to discontinue OPSUMIT.

5.4 Hemoglobin Decrease

Decreases in hemoglobin concentration and hematocrit have occurred following administration of other ERAs and were observed in clinical studies with OPSUMIT. These decreases occurred early and stabilized thereafter. In the placebo-controlled study of OPSUMIT in PAH, OPSUMIT 10 mg caused a mean decrease in hemoglobin from baseline to up to 18 months of about 1.0 g/dL compared to no change in the placebo group. A decrease in hemoglobin to below 10.0 g/dL was reported in 8.7% of the OPSUMIT 10 mg group and in 3.4% of the placebo group. Decreases in hemoglobin seldom require transfusion. Initiation of OPSUMIT is not recommended in patients with severe anemia. Measure hemoglobin prior to initiation of treatment and repeat during treatment as clinically indicated [see Adverse Reactions (6.1)] .

5.5 Pulmonary Edema with Pulmonary Veno-occlusive Disease (PVOD)

Should signs of pulmonary edema occur, consider the possibility of associated PVOD. If confirmed, discontinue OPSUMIT.

5.6 Decreased Sperm Counts

OPSUMIT, like other ERAs, may have an adverse effect on spermatogenesis. Counsel men about potential effects on fertility [see Use in Specific Populations (8.3) and Nonclinical Toxicology (13.1)] .

6 ADVERSE REACTIONS

Clinically significant adverse reactions that appear in other sections of the labeling include:

- Embryo-fetal Toxicity [see Warnings and Precautions (5.1)]
- Hepatotoxicity [see Warnings and Precautions (5.2)]
- Fluid Retention [see Warnings and Precautions (5.3)]
- Decrease in Hemoglobin [see Warnings and Precautions (5.4)]

6.1 Clinical Trial Experience

Because clinical trials are conducted under widely varying conditions, adverse reaction rates observed in clinical trials of a drug cannot be directly compared to rates in the clinical trials of another drug and may not reflect the rates observed in clinical practice.

Safety data for OPSUMIT were obtained primarily from one placebo-controlled clinical study in 742 patients with PAH (SERAPHIN study) [see Clinical Studies (14.1)].

The exposure to OPSUMIT in this trial was up to 3.6 years with a median exposure of about 2 years (N=542 for 1 year; N=429 for 2 years; and N=98 for more than 3 years). The overall incidence of treatment discontinuations because of adverse events was similar across OPSUMIT 10 mg and placebo treatment groups (approximately 11%).

Table 2 presents adverse reactions more frequent on OPSUMIT than on placebo by ≥3%.

Table 2: Adverse Reactions
Adverse Reaction | OPSUMIT 10 mg (N=242) (%) | Placebo (N=249) (%)
Anemia | 13 | 3
Nasopharyngitis/pharyngitis | 20 | 13
Bronchitis | 12 | 6
Headache | 14 | 9
Influenza | 6 | 2
Urinary tract infection | 9 | 6

6.2 Postmarketing Experience

The following adverse reactions have been identified during post-approval use of OPSUMIT. Because these reactions are reported voluntarily from a population of uncertain size, it is not always possible to reliably estimate their frequency or establish a causal relationship to drug exposure.

Immune system disorders:hypersensitivity reactions (angioedema, pruritus and rash)

Vascular disorders: flushing

Respiratory, thoracic and mediastinal disorders: nasal congestion

Gastrointestinal disorders: Elevations of liver aminotransferases (ALT, AST) and liver injury have been reported with OPSUMIT use; in most cases alternative causes could be identified (heart failure, hepatic congestion, autoimmune hepatitis). Endothelin receptor antagonists have been associated with elevations of aminotransferases, hepatotoxicity, and cases of liver failure [see Warnings and Precautions (5.2)] .

General disorders and administration site conditions:edema/fluid retention. Cases of edema and fluid retention occurred within weeks of starting OPSUMIT, some requiring intervention with a diuretic, fluid management or hospitalization for decompensated heart failure [see Warnings and Precautions (5.3)].

Cardiac disorders: symptomatic hypotension

7 DRUG INTERACTIONS

7.1 Strong CYP3A4 Inducers

Strong inducers of CYP3A4 such as rifampin significantly reduce macitentan exposure. Concomitant use of OPSUMIT with strong CYP3A4 inducers should be avoided [see Clinical Pharmacology (12.3)] .

7.2 Strong CYP3A4 Inhibitors

Concomitant use of strong CYP3A4 inhibitors like ketoconazole approximately double macitentan exposure. Many HIV drugs like ritonavir are strong inhibitors of CYP3A4. Avoid concomitant use of OPSUMIT with strong CYP3A4 inhibitors [see Clinical Pharmacology (12.3)] . Use other PAH treatment options when strong CYP3A4 inhibitors are needed as part of HIV treatment [see Clinical Pharmacology (12.3)] .

7.3 Moderate Dual or Combined CYP3A4 and CYP2C9 Inhibitors

Concomitant use of moderate dual inhibitors of CYP3A4 and CYP2C9 such as fluconazole is predicted to increase macitentan exposure approximately 4-fold based on physiologically based pharmacokinetic (PBPK) modeling. Avoid concomitant use of OPSUMIT with moderate dual inhibitors of CYP3A4 and CYP2C9 (such as fluconazole and amiodarone) [see Clinical Pharmacology (12.3)] .

Concomitant treatment of both a moderate CYP3A4 inhibitor and moderate CYP2C9 inhibitor with OPSUMIT should also be avoided [see Clinical Pharmacology (12.3)].

8 USE IN SPECIFIC POPULATIONS

8.1 Pregnancy

Risk Summary

Based on data from animal reproduction studies, OPSUMIT may cause embryo-fetal toxicity, including birth defects and fetal death, when administered to a pregnant female and is contraindicated during pregnancy. There are risks to the mother and the fetus associated with pulmonary arterial hypertension in pregnancy [see Clinical Considerations] . Available data from postmarketing reports and published literature over decades of use with ERAs in the same class as OPSUMIT have not identified an increased risk of major birth defects; however, these data are limited. Methodological limitations of these postmarketing reports and published literature include lack of a control group; limited information regarding dose, duration, and timing of drug exposure; and missing data. These limitations preclude establishing a reliable estimate of the risk of adverse fetal and neonatal outcomes with maternal ERA use. Macitentan was teratogenic in rabbits and rats at all doses tested. If this drug is used during pregnancy, or if the patient becomes pregnant while taking this drug, advise the patient of the risk to a fetus [see Contraindications (4.1)] .

The estimated background risk of major birth defects and miscarriage for the indicated population is unknown. All pregnancies have a background risk of birth defect, loss, or other adverse outcomes. In the U.S. general population, the estimated background risk of major birth defects and miscarriage in clinically recognized pregnancies is 2–4% and 15–20%, respectively.

Clinical Considerations

Disease-associated Maternal and/or Embryo/Fetal Risk

In patients with pulmonary arterial hypertension, pregnancy is associated with an increased rate of maternal and fetal morbidity and mortality, including spontaneous abortion, intrauterine growth restriction and premature labor.

Data

Animal Data

In both rabbits and rats, there were cardiovascular and mandibular arch fusion abnormalities. Administration of macitentan to female rats from late pregnancy through lactation caused reduced pup survival and impairment of the male fertility of the offspring at all dose levels tested.

8.2 Lactation

Risk Summary

There are no data on the presence of macitentan in human milk, the effects on the breastfed infant, or the effect on milk production. Because of the potential for serious adverse reactions in breastfed infants from OPSUMIT advise women not to breastfeed during treatment with OPSUMIT.

8.3 Females and Males of Reproductive Potential

Based on data from animal reproductive toxicity studies, OPSUMIT can cause fetal harm, including birth defects and fetal death, when administered to a pregnant patient and is contraindicated during pregnancy [see Contraindications (4.1), and Use in Specific Populations (8.1)].

Pregnancy Testing

Verify that patients who can become pregnant are not pregnant prior to initiating OPSUMIT. The patient should contact their physician immediately for pregnancy testing if onset of menses is delayed or pregnancy is suspected. If the pregnancy test is positive, the physician and patient should discuss the risks to the pregnancy, and the fetus.

Contraception

Patients who can become pregnant who are using OPSUMIT should use an effective method of contraception prior to initiation of treatment, during treatment, and for one month after discontinuation of treatment with OPSUMIT to prevent pregnancy [see Warnings and Precautions (5.1)] .

Infertility

Based on findings in animals, OPSUMIT may impair fertility in males of reproductive potential. It is not known whether effects on fertility would be reversible [see Warnings and Precautions (5.6), Adverse Reactions (6.1), and Nonclinical Toxicology (13.1)] .

8.4 Pediatric Use

The safety and effectiveness of OPSUMIT in pediatric patients have not been established for the treatment of PAH.

OPSUMIT was evaluated in 148 pediatric patients 2 to 17 years of age with PAH in a single open-label, randomized trial with an extension period in which all patients received treatment. The trial did not demonstrate a clinical benefit of OPSUMIT compared with standard of care in the treatment of PAH. It cannot be ruled out that a trial with a different design would demonstrate a clinical benefit in this patient population. Adverse reactions observed in the trial were similar in nature to those reported in clinical trials in adults.

8.5 Geriatric Use

Of the total number of subjects in the clinical study of OPSUMIT for PAH, 14% were 65 and over. No overall differences in safety or effectiveness were observed between these subjects and younger subjects.

10 OVERDOSAGE

OPSUMIT has been administered as a single dose of up to and including 600 mg to healthy subjects (60 times the approved dosage). Adverse reactions of headache, nausea and vomiting were observed. In the event of an overdose, standard supportive measures should be taken, as required. Dialysis is unlikely to be effective because macitentan is highly protein-bound.

11 DESCRIPTION

OPSUMIT® (macitentan) is an endothelin receptor antagonist. The chemical name of macitentan is N-[5-(4-Bromophenyl)-6-[2-[(5-bromo-2-pyrimidinyl)oxy]ethoxy]-4-pyrimidinyl]-N'-propylsulfamide. It has a molecular formula of C19H20Br2N6O4S and a molecular weight of 588.27. Macitentan is achiral and has the following structural formula:

Macitentan is a crystalline powder that is insoluble in water. In the solid state macitentan is very stable, is not hygroscopic, and is not light sensitive.

OPSUMIT is available as a 10 mg film-coated tablet for once daily oral administration. The tablets include the following inactive ingredients: lactose monohydrate, magnesium stearate, microcrystalline cellulose, polysorbate 80, povidone, and sodium starch glycolate Type A. The tablets are film-coated with a coating material containing polyvinyl alcohol, soya lecithin, talc, titanium dioxide, and xanthan gum.

13 NONCLINICAL TOXICOLOGY

13.1 Carcinogenesis, Mutagenesis, Impairment of Fertility

Carcinogenesis

Carcinogenicity studies of 2 years' duration did not reveal any carcinogenic potential at exposures 75-fold and 140-fold the human exposure (based on AUC) in male and female mice, respectively, and 8.3- and 42-fold in male and female rats, respectively.

Mutagenesis

Macitentan was not genotoxic in a standard battery of in vitro and in vivo assays that included a bacterial reverse mutation assay, an assay for gene mutations in mouse lymphoma cells, a chromosome aberration test in human lymphocytes, and an in vivo micronucleus test in rats.

Impairment of Fertility

Reversible testicular tubular dilatation was observed in chronic toxicity studies at exposures greater than 7-fold and 23-fold the human exposure in rats and dogs, respectively. After 2 years of treatment, tubular atrophy was seen in rats at 4-fold the human exposure. Macitentan did not affect male or female fertility at exposures ranging from 19- to 44-fold the human exposure, respectively, and had no effect on sperm count, motility, and morphology in male rats. No testicular findings were noted in mice after treatment up to 2 years.

13.2 Animal Toxicology

In dogs, macitentan decreased blood pressure at exposures similar to the therapeutic human exposure. Intimal thickening of coronary arteries was observed at 17-fold the human exposure after 4 to 39 weeks of treatment. Due to the species-specific sensitivity and the safety margin, this finding is considered not relevant for humans.

There were no adverse liver findings in long-term studies conducted in mice, rats, and dogs at exposures of 12- to 116-fold the human exposure.

12 CLINICAL PHARMACOLOGY

12.1 Mechanism of Action

Endothelin (ET)-1 and its receptors (ETA and ETB) mediate a variety of deleterious effects, such as vasoconstriction, fibrosis, proliferation, hypertrophy, and inflammation. In disease conditions such as PAH, the local ET system is upregulated and is involved in vascular hypertrophy and in organ damage.

Macitentan is an endothelin receptor antagonist that inhibits the binding of ET-1 to both ETA and ETB receptors. Macitentan displays high affinity and sustained occupancy of the ET receptors in human pulmonary arterial smooth muscle cells. One of the metabolites of macitentan is also pharmacologically active at the ET receptors and is estimated to be about 20% as potent as the parent drug in vitro. The clinical impact of dual endothelin blockage is unknown.

12.2 Pharmacodynamics

Pulmonary Hemodynamics

The clinical efficacy study in patients with pulmonary arterial hypertension assessed hemodynamic parameters in a subset of patients after 6 months of treatment. Patients treated with OPSUMIT 10 mg (N=57) achieved a median reduction of 37% (95% CI 22–49) in pulmonary vascular resistance and an increase of 0.6 L/min/m^2 (95% CI 0.3–0.9) in cardiac index compared to placebo (N=67).

Cardiac Electrophysiology

In a randomized, placebo-controlled four-way crossover study with a positive control in healthy subjects, repeated doses of macitentan 10 and 30 mg (3 times the recommended dosage) had no significant effect on the QTc interval.

12.3 Pharmacokinetics

The pharmacokinetics of macitentan and its active metabolite have been studied primarily in healthy subjects. The pharmacokinetics of macitentan are dose proportional over a range from 1 mg to 30 mg after once daily administration.

A cross study comparison shows that the exposures to macitentan and its active metabolite in patients with PAH are similar to those observed in healthy subjects.

Absorption and Distribution

The maximum plasma concentration of macitentan is achieved about 8 hours after oral administration. The absolute bioavailability after oral administration is not known. In a study in healthy subjects, the exposure to macitentan and its active metabolite were unchanged after a high fat breakfast. Macitentan may therefore be taken with or without food.

Macitentan and its active metabolite are highly bound to plasma proteins (>99%), primarily to albumin and to a lesser extent to alpha-1-acid glycoprotein. The apparent volumes of distribution (Vss/F) of macitentan and its active metabolite were about 50 L and 40 L respectively in healthy subjects.

Metabolism and Elimination

Following oral administration, the apparent elimination half-lives of macitentan and its active metabolite are approximately 16 hours and 48 hours, respectively. Macitentan is metabolized primarily by oxidative depropylation of the sulfamide to form the pharmacologically active metabolite. This reaction is dependent on the cytochrome P450 (CYP) system, mainly CYP3A4 with minor contributions of CYP2C8, CYP2C9, and CYP2C19. At steady state in PAH patients, the systemic exposure to the active metabolite is 3-times the exposure to macitentan and is expected to contribute approximately 40% of the total pharmacologic activity. In a study in healthy subjects with radiolabeled macitentan, approximately 50% of radioactive drug material was eliminated in urine but none was in the form of unchanged drug or the active metabolite. About 24% of the radioactive drug material was recovered from feces.

Special Populations

There are no clinically relevant effects of age, sex, or race on the pharmacokinetics of macitentan and its active metabolite.

Renal Impairment

Exposure to macitentan and its active metabolite in patients with severe renal impairment (CrCl 15–29 mL/min) compared to healthy subjects was increased by 30% and 60%, respectively. This increase is not considered clinically relevant.

Hepatic Impairment

Exposure to macitentan was decreased by 21%, 34%, and 6% and exposure to the active metabolite was decreased by 20%, 25%, and 25% in subjects with mild, moderate, or severe hepatic impairment (Child-Pugh Class A, B, and C), respectively. This decrease is not considered clinically relevant.

Drug Interactions

In Vitro Studies

At plasma levels obtained with dosing at 10 mg once daily, macitentan has no relevant inhibitory or inducing effects on CYP enzymes. Macitentan is not a substrate or inhibitor of multi-drug resistance protein (P-gp, MDR-1). The active metabolite of macitentan also is not an inhibitor of P-gp/MDR-1 at clinically relevant concentrations.

Macitentan and its active metabolite are not expected to have significant interaction with drug transporters such as organic anion transporting polypeptide (OATP1B1, OATP1B3), multidrug and toxin extrusion protein (MATE-1, MATE-2K), bile salt export pump (BSEP), sodium-taurocholate co-transporting polypeptide (NTCP), organic cation transporter (OCT-1, OCT-3), organic anion transporter (OAT-1, OAT-3) or BCRP transporter at clinically relevant plasma concentrations.

In Vivo Studies

Effect of other drugs on macitentan

The effect of other drugs on macitentan and its active metabolite are studied in healthy subjects and are shown in Figure 1 below.

Figure 1

Effects of other strong CYP3A4 inhibitors such as ritonavir on macitentan were not studied, but are likely to result in an increase in macitentan exposure at steady state similar to that seen with ketoconazole [see Drug Interactions (7.2)] .

PBPK modeling and simulations based analysis showed that a moderate dual inhibitor of CYP3A4 and CYP2C9 such as fluconazole (400 mg once daily) is predicted to increase macitentan exposure approximately 4-fold without relevant effect on the exposure to its active metabolite [see Drug Interactions (7.3)] .

Effect of macitentan on other drugs

Warfarin: Macitentan once daily dosing did not alter the exposure to R- and S-warfarin or their effect on international normalized ratio (INR).

Sildenafil: At steady-state, the exposure to sildenafil 20 mg t.i.d. increased by 15% during concomitant administration of macitentan 10 mg once daily. This change is not considered clinically relevant.

Hormonal contraceptives: Macitentan 10 mg once daily did not affect the pharmacokinetics of an oral contraceptive (norethisterone 1 mg and ethinyl estradiol 35 µg).

BCRP Substrate drugs: Macitentan 10 mg once daily did not affect the pharmacokinetics of concomitant use of a BCRP substrate drug (riociguat 1 mg and rosuvastatin 10 mg).

14 CLINICAL STUDIES

14.1 Pulmonary Arterial Hypertension

The effect of macitentan on progression of PAH was demonstrated in a multi-center, long-term (average duration of exposure approximately 2 years), placebo-controlled study in 742 patients with symptomatic [WHO functional class (FC) II–IV] PAH who were randomized to placebo (n=250), 3 mg macitentan (n=250), or 10 mg macitentan (n=242) once daily. Patients were treated with OPSUMIT monotherapy or in combination with phosphodiesterase-5 inhibitors or inhaled prostanoids.

The primary study endpoint was time to the first occurrence of death, a significant morbidity event, defined as atrial septostomy, lung transplantation, initiation of IV or subcutaneous (SC) prostanoids, or "other worsening of PAH" during double-blind treatment plus 7 days. Other worsening was defined as all of the following: 1) a sustained ≥15% decrease from baseline in 6 minute walk distance (6MWD), 2) worsening of PAH symptoms (worsening of WHO FC), and 3) need for additional treatment for PAH. All of these other worsening events were confirmed by an independent adjudication committee, blinded to treatment allocation. A critical secondary endpoint was time to PAH death or PAH hospitalization.

The mean patient age was 46 years (14% were age 65 or above). Most patients were white (55%) or Asian (29%) and female (77%). Approximately 52%, 46%, and 2% of patients were in WHO FC II, III, and IV, respectively.

Idiopathic or heritable PAH was the most common etiology in the study population (57%) followed by PAH caused by connective tissue disorders (31%), PAH caused by congenital heart disease with repaired shunts (8%), and PAH caused by other etiologies [drugs and toxins (3%) and HIV (1%)].

At baseline, the majority of enrolled patients (64%) were being treated with a stable dose of specific therapy for PAH, either oral phosphodiesterase inhibitors (61%) and/or inhaled/oral prostanoids (6%).

Study results are described for the placebo and OPSUMIT 10 mg groups. The median treatment durations were 101 and 118 weeks in the placebo and OPSUMIT 10 mg groups, respectively, up to a maximum of 188 weeks.

Treatment with OPSUMIT 10 mg resulted in a 45% reduction (HR 0.55, 97.5% CI 0.39–0.76; logrank p<0.0001) in the occurrence of the primary endpoint up to end of double-blind treatment compared to placebo (Table 3 and Figure 2). The beneficial effect of OPSUMIT 10 mg was primarily attributable to a reduction in clinical worsening events (deterioration in 6MWD and worsening of PAH symptoms and need for additional PAH treatment).

Figure 2 Kaplan-Meier Estimates of the Occurrence of the Primary Endpoint Event in the SERAPHIN Study

Table 3: Summary of Primary Endpoint Events
 | Placebo N=250 n (%) | OPSUMIT 10 mg N=242 n (%)
Patients with a primary endpoint event [No patients experienced an event of lung transplantation or atrial septostomy in the placebo or OPSUMIT 10 mg treatment groups.] | 116 (46.4) | 76 (31.4)
Component as first event
Worsening PAH | 93 (37.2) | 59 (24.4)
Death | 17 (6.8) | 16 (6.6)
IV/SC prostanoid | 6 (2.4) | 1 (0.4)

Subgroup analyses were performed to examine their influence on outcome as shown in Figure 3. Consistent efficacy of OPSUMIT 10 mg on the primary endpoint was seen across subgroups of age, sex, race, etiology, by monotherapy or in combination with another PAH therapy, baseline 6MWD, and baseline WHO FC.

Figure 3 Subgroup Analysis of the SERAPHIN Study

Eo = Number of events OPSUMIT 10 mg; No = Number of patients randomized to OPSUMIT 10 mg
Ep = Number of events placebo; Np = Number of patients randomized to placebo

PAH related death or hospitalization for PAH was assessed as a secondary endpoint. The risk of PAH related death or hospitalization for PAH was reduced by 50% in patients receiving OPSUMIT 10 mg compared to placebo (HR 0.50, 97.5% CI 0.34–0.75; logrank p<0.0001) (Table 4 and Figure 4).

Figure 4 Kaplan-Meier Estimates of the Occurrence of Death due to PAH or Hospitalization for PAH in SERAPHIN

Table 4: Summary of Death due to PAH and Hospitalization due to PAH
 | Placebo (N=250) n (%) | OPSUMIT 10 mg (N=242) n (%)
Death due to PAH or hospitalization for PAH | 84 (33.6) | 50 (20.7)
Component as first event
Death due to PAH | 5 (2.0) | 5 (2.1)
Hospitalization for PAH | 79 (31.6) | 45 (18.6)

Treatment with OPSUMIT 10 mg resulted in a placebo-corrected mean increase in 6MWD of 22 meters at Month 6 (97.5% CI 3–41; p=0.0078), with significant improvement in 6MWD by Month 3. 6MWD increased more in patients with worse baseline WHO Functional Class (37 meters and 12 meters placebo-corrected mean increase in WHO FC III/IV and FC I/II, respectively). The increase in 6MWD achieved with OPSUMIT was maintained for the duration of the study.

Treatment with OPSUMIT 10 mg led to an improvement of at least one WHO Functional Class at Month 6 in 22% of patients compared to 13% of patients treated with placebo.

Long-Term Treatment of PAH

In long-term follow-up of patients who were treated with OPSUMIT 10 mg in the placebo-controlled study (N=242) and the open-label extension study, Kaplan-Meier estimates of survival at 1, 2, 5, and 7 years were 95%, 89%, 73%, and 63% respectively. The median exposure to OPSUMIT was 4.6 years. These uncontrolled observations do not allow comparison with a group not given OPSUMIT and cannot be used to determine the long term-effect of OPSUMIT on mortality.

16 HOW SUPPLIED/STORAGE AND HANDLING

OPSUMIT® (macitentan) tablets are 10 mg white, film-coated, bi-convex debossed with "10" on both sides and supplied as follows:

15 count /PVC/ PE/PVDC aluminum foil blisters in carton (NDC 66215-501-15)

30 count white high-density polyethylene bottle in carton (NDC 66215-501-30)

STORAGE AND HANDLING

Store at 20 ºC to 25 ºC (68 ºF to 77 ºF). Excursions are permitted between 15 °C and 30 °C (59 °F and 86 °F). [See USP Controlled Room Temperature].

Keep out of reach of children.

17 PATIENT COUNSELING INFORMATION

Advise patient to read FDA-approved patient labeling (Medication Guide).

Embryo-Fetal Toxicity

Counsel female patients of reproductive potential about the need to use effective methods of contraception prior to initiation of treatment with OPSUMIT, during treatment and for one month after treatment discontinuation. Females of reproductive potential should have a negative pregnancy test prior to treatment with OPSUMIT [see Contraindications (4.1), and Use in Specific Populations (8.1, 8.3)] .

Patients should be instructed to contact their physician if they suspect they may be pregnant. Patients should seek additional contraceptive advice from a gynecologist or similar expert as needed.

Educate and counsel females of reproductive potential on the use of emergency contraception in the event of unprotected sex or contraceptive failure.

Advise pre-pubertal females to report any changes in their reproductive status immediately to her prescriber.

Review the Medication Guide with female patients.

Lactation

Advise women not to breastfeed during treatment with OPSUMIT [see Use in Specific Populations (8.2)] .

Hepatotoxicity

Some members of this pharmacological class are hepatotoxic. Educate patients on signs of hepatotoxicity. Advise patients that they should contact their doctor if they have unexplained nausea, vomiting, right upper quadrant pain, fatigue, anorexia, jaundice, dark urine, fever, or itching [see Warnings and Precautions (5.2)].

Fluid Retention

Educate patients on signs of fluid retention. Advise patients that they should contact their doctor if they have unusual weight increase or swelling of the ankles or legs [see Warnings and Precautions (5.3)] .

Manufactured for:

Actelion Pharmaceuticals US, Inc.
Titusville, NJ 08560, USA

For patent information: www.janssenpatents.com

© Johnson & Johnson and its affiliates 2013 – 2019.

MEDICATION GUIDE
OPSUMIT® (OP-sum-it)
(macitentan)
tablets

Read this Medication Guide for OPSUMIT before you start taking OPSUMIT and each time you get a refill. There may be new information. This Medication Guide does not take the place of talking with your healthcare provider about your medical condition or your treatment.

What is the most important information I should know about OPSUMIT?

- Serious birth defects.

OPSUMIT can cause serious birth defects if taken during pregnancy.

- Females should not be pregnant when they start taking OPSUMIT or become pregnant during treatment with OPSUMIT.
- Females who are able to get pregnant should have a negative pregnancy test before beginning treatment with OPSUMIT. Talk to your healthcare provider about your menstrual cycle. Your healthcare provider will decide when to do the pregnancy test and will order a pregnancy test for you depending on your menstrual cycle.
  - Females who are able to get pregnant are females who:
    - have entered puberty, even if they have not started their menstrual period, and
    - have a uterus, and
    - have not gone through menopause. Menopause means that you have not had a menstrual period for at least 12 months for natural reasons, or that you have had your ovaries removed.
  - Females who are not able to get pregnant are females who:
    - have not yet entered puberty, or
    - do not have a uterus, or
    - have gone through menopause. Menopause means that you have not had a menstrual period for at least 12 months for natural reasons, or that you have had your ovaries removed, or
    - are infertile for other medical reasons and this infertility is permanent and cannot be reversed.

Females who are able to get pregnant should use effective birth control before starting treatment with OPSUMIT, during treatment, and for one month after stopping OPSUMIT because the medicine may still be in the body.

- Talk with your healthcare provider or gynecologist (a doctor who specializes in female reproduction) to find out about options for acceptable birth control that you may use to prevent pregnancy during treatment with OPSUMIT.
- If you decide that you want to change the form of birth control that you use, talk with your healthcare provider or gynecologist to be sure that you choose another acceptable form of birth control.
- Do not have unprotected sex. Talk to your healthcare provider or pharmacist right away if you have unprotected sex or if you think your birth control has failed. Your healthcare provider may talk with you about using emergency birth control.
- Tell your healthcare provider right away if you miss a menstrual period or think you may be pregnant.

If you are the parent or caregiver of a female child who started taking OPSUMIT before reaching puberty, you should check your child regularly to see if she is developing signs of puberty. Tell your healthcare provider right away if you notice that she is developing breast buds or any pubic hair. Your healthcare provider should decide if your child has reached puberty. Your child may reach puberty before having her first menstrual period.
If you are a female who can get pregnant, you should talk to your healthcare provider to understand the benefits and risks of OPSUMIT.

What is OPSUMIT?

- OPSUMIT is a prescription medicine used to treat pulmonary arterial hypertension (PAH), which is high blood pressure in the arteries of your lungs.
- OPSUMIT can improve your ability to exercise, improve some of your symptoms, and help slow down the progression of your disease. OPSUMIT can also lower your chance of being hospitalized for PAH.
- It is not known if OPSUMIT is safe and effective in children.

Who should not take OPSUMIT?

Do not take OPSUMIT if you are pregnant, plan to become pregnant, or become pregnant during treatment with OPSUMIT. OPSUMIT can cause serious birth defects (see the Medication Guide section above called " What is the most important information I should know about OPSUMIT?").
Do not take OPSUMIT if you are allergic to macitentan or any of the ingredients in OPSUMIT. See the end of this Medication Guide for a complete list of ingredients in OPSUMIT.

Tell your healthcare provider about all your medical conditions and all the medicines you take, including prescription and over-the-counter medicines, vitamins, and herbal supplements. OPSUMIT and other medicines may affect each other causing side effects. Do not start any new medicine until you check with your healthcare provider.

Especially tell your healthcare provider if you take an HIV medicine.

How should I take OPSUMIT?

OPSUMIT will be mailed to you by a specialty pharmacy. Your healthcare provider will give you complete details.

- Take OPSUMIT exactly as your healthcare provider tells you to take it. Do not stop taking OPSUMIT unless your healthcare provider tells you.
- You can take OPSUMIT with or without food.
- If you take too much OPSUMIT, call your healthcare provider or go to the nearest hospital emergency room right away.
- If you miss a dose of OPSUMIT, take it as soon as you remember that day. Take the next dose at your regular time. Do not take 2 doses at the same time to make up for a missed dose.

What should I avoid while taking OPSUMIT?

- Do not get pregnant while taking OPSUMIT. See the serious birth defects section of the Medication Guide above called " What is the most important information I should know about OPSUMIT?" If you miss a menstrual period, or think you might be pregnant, call your healthcare provider right away.
- It is not known if OPSUMIT passes into your breastmilk. You should not breastfeed if you take OPSUMIT. Talk to your healthcare provider about the best way to feed your baby if you take OPSUMIT.

What are the possible side effects of OPSUMIT?

OPSUMIT can cause serious side effects, including:

- Serious birth defects. See " What is the most important information I should know about OPSUMIT?"
- Some medicines that are like OPSUMIT can cause liver problems. Your healthcare provider should do blood tests to check your liver before you start taking OPSUMIT. Tell your healthcare provider if you have any of the following symptoms of liver problems while taking OPSUMIT.

- nausea or vomiting
- pain in the upper right stomach
- tiredness
- loss of appetite

- yellowing of your skin or whites of your eyes
- dark urine
- fever
- itching

- Fluid retention can happen within weeks after starting OPSUMIT. Tell your healthcare provider right away if you have any unusual weight gain or swelling of your ankles or legs. Your healthcare provider will look for the cause of any fluid retention.
- Low red blood cell levels (anemia) can occur with OPSUMIT treatment, usually during the first weeks after starting therapy. In some cases a blood transfusion may be needed, but this is not common. Your healthcare provider will do blood tests to check your red blood cells before starting OPSUMIT. Your healthcare provider may also need to do these tests during treatment with OPSUMIT.
- Decreased sperm count. OPSUMIT, and other medicines like OPSUMIT, may cause decreased sperm counts in men who take these medicines. A decreased sperm count may affect the ability to father a child. Tell your healthcare provider if being able to have children is important to you.

The most common side effects of OPSUMIT are:

- Stuffy nose or sore throat
- Irritation of the airways (bronchitis)
- Headache
- Flu
- Urinary tract infection

Tell your healthcare provider if you have any side effect that bothers you or that does not go away. These are not all the possible side effects of OPSUMIT. For more information, ask your healthcare provider or pharmacist.

Call your healthcare provider for medical advice about side effects. You may report side effects to FDA at 1-800-FDA-1088.

How should I store OPSUMIT?

- Store OPSUMIT tablets at room temperature between 68 °F and 77 °F (20 °C and 25 °C).
- Keep OPSUMIT and all medicines out of the reach of children.

General information about OPSUMIT

Medicines are sometimes prescribed for purposes other than those listed in a Medication Guide. Do not use OPSUMIT for a condition for which it was not prescribed. Do not give OPSUMIT to other people, even if they have the same symptoms that you have. It may harm them.

This Medication Guide summarizes the most important information about OPSUMIT. If you would like more information, talk with your healthcare provider. You can ask your pharmacist or healthcare provider for information about OPSUMIT that is written for health professionals. For more information, call 1-800-526-7736, or visit www.OPSUMIT.com.

What are the ingredients in OPSUMIT?

Active ingredient: macitentan

Inactive ingredients: lactose monohydrate, magnesium stearate, microcrystalline cellulose, polysorbate 80, povidone, and sodium starch glycolate Type A. The tablets are film-coated with a coating material containing polyvinyl alcohol, soya lecithin, talc, titanium dioxide, and xanthan gum.

Manufactured for:
Actelion Pharmaceuticals US, Inc.
Titusville, NJ 08560, USA
For patent information: www.janssenpatents.com
© Johnson & Johnson and its affiliates 2013 – 2019.

This Medication Guide has been approved by the U.S. Food and Drug Administration.

Revised: 4/2025

PRINCIPAL DISPLAY PANEL - 10 mg Tablet Bottle Carton

NDC 66215-501-30

Opsumit®
(macitentan) tablets

10 mg

Dispense the
accompanying
Medication Guide
to each patient

Rx only
30 film-coated tablets

janssen